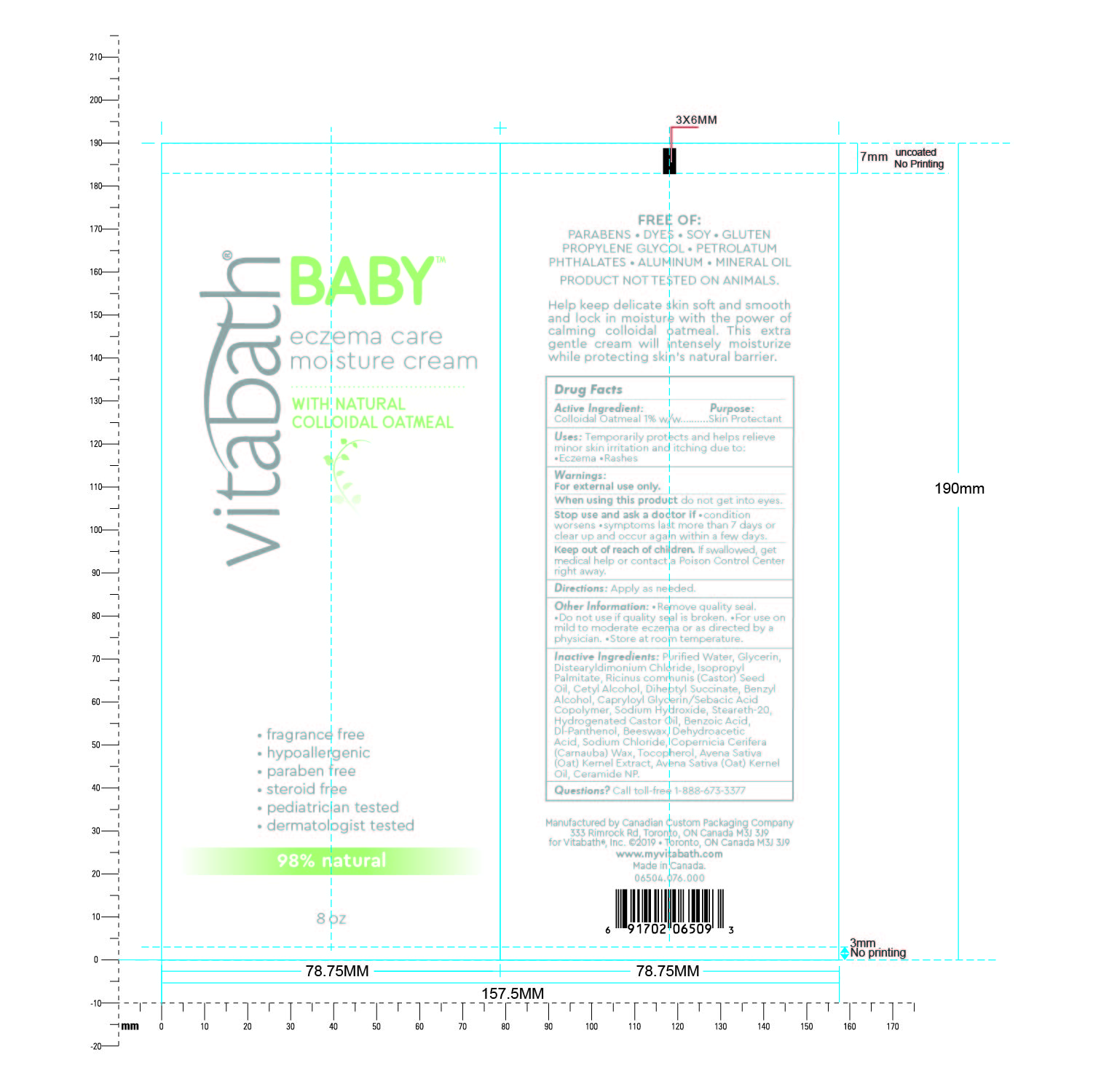 DRUG LABEL: Vitabath Baby Eczema Care Moisture
NDC: 73172-001 | Form: CREAM
Manufacturer: Vitabath, Inc.
Category: otc | Type: HUMAN OTC DRUG LABEL
Date: 20190611

ACTIVE INGREDIENTS: OATMEAL 1 g/100 g
INACTIVE INGREDIENTS: HYDROGENATED CASTOR OIL; BENZOIC ACID; PANTHENOL; YELLOW WAX; SODIUM CHLORIDE; TOCOPHEROL; OAT; OAT KERNEL OIL; CERAMIDE NP; SODIUM HYDROXIDE; WATER; GLYCERIN; DISTEARYLDIMONIUM CHLORIDE; ISOPROPYL PALMITATE; STEARETH-20; CASTOR OIL; CETYL ALCOHOL; DIHEPTYL SUCCINATE; BENZYL ALCOHOL; CAPRYLOYL GLYCERIN/SEBACIC ACID COPOLYMER (2000 MPA.S); DEHYDROACETIC ACID; CARNAUBA WAX

Vitabath Baby Eczema Care Moisture Cream

Active Ingredients

Colloidal Oatmeal 1% w/w

Purpose

Skin protectant

Uses

Temporarily protects and helps relieve minor skin irritation and itching due to •Eczema •Rashes

Warnings

For external use only.

When using this product

- Avoid contact with eyes

When using this product do not get into eyes.

Stop use and ask a doctor if

- CONDITIONS WORSENS
- SYMPTOMS LAST MORE THAN 7 DAYS OR CLEAR UP AND OCCUR AGAIN WITHIN A FEW DAYS.

KEEP OUT OF REACH OF CHILDREN. If swallowed, get medical help or contact a Poison Control Center right away.

Directions

Apply as needed.

OTHER INFORMATION:

•Remove quality seal •Do not use if quality seal is broken •For use on mild to moderate eczema or as directed by a physician •Store at room temperature

Inactive Ingredients

Purified water
Glycerin
Distearyldimonium Chloride
Isopropyl Palmitate
Ricinus communis (Castor) Seed Oil
Cetyl Alcohol
Diheptyl Succinate
Benzyl Alcohol
Capryloyl Glycerin/Sebacic Acid Copolymer
Sodium Hydroxide
Steareth-20
Hydrogenated Castor Oil
Benzoic Acid
Dl-Panthenol
Beeswax
Dehydroacetic Acid
Sodium Chloride
Copernicia Cerifera (Carnauba) Wax
Tocopherol
Avena Sativa (Oat) Kernel Extract
Avena Sativa (Oat) Kernel Oil
Ceramide NP

Questions? Call toll-free 1-888-673-3377